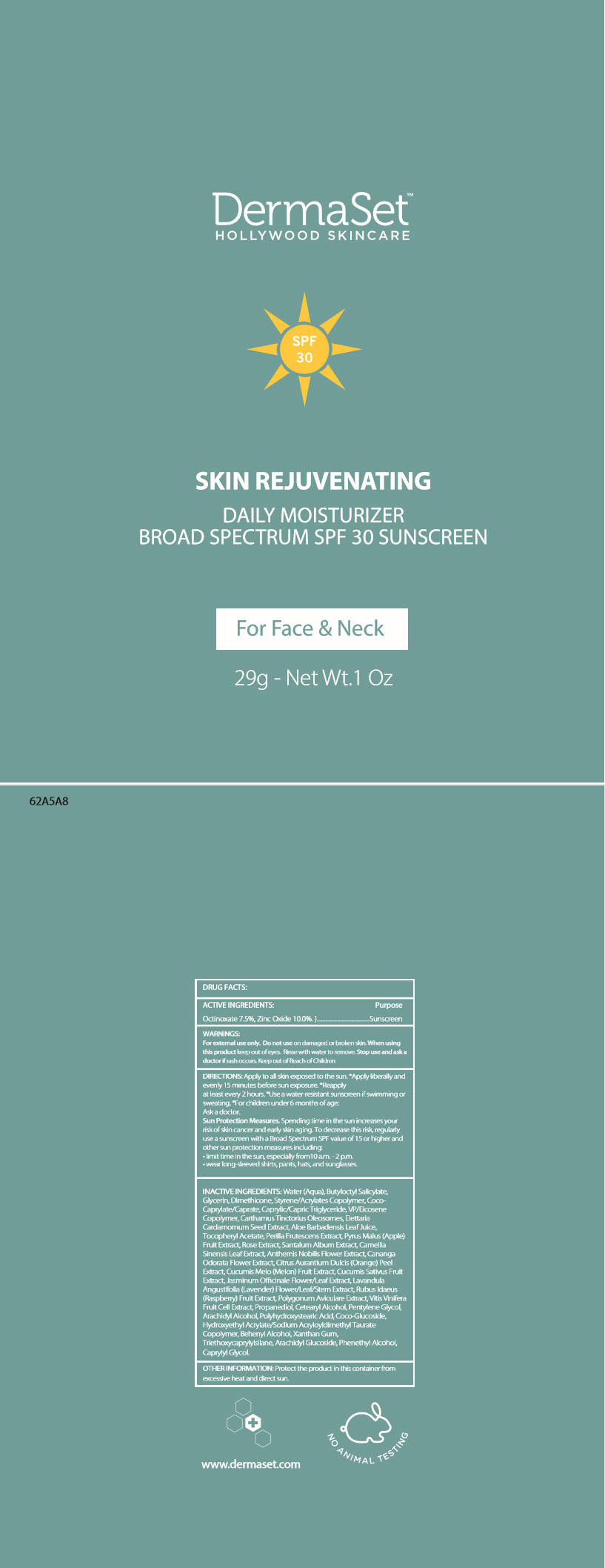 DRUG LABEL: SKIN REJUVENATING DAILY MOISTURIZER BROAD SPECTRUM SPF 30 SUNSCREEN
NDC: 80873-100 | Form: CREAM
Manufacturer: Dermaset, Inc.
Category: otc | Type: HUMAN OTC DRUG LABEL
Date: 20220114

ACTIVE INGREDIENTS: OCTINOXATE 75 mg/1 g; ZINC OXIDE 100 mg/1 g
INACTIVE INGREDIENTS: WATER; BUTYLOCTYL SALICYLATE; GLYCERIN; DIMETHICONE; STYRENE/ACRYLAMIDE COPOLYMER (500000 MW); COCOYL CAPRYLOCAPRATE; MEDIUM-CHAIN TRIGLYCERIDES; CARTHAMUS TINCTORIUS SEED OLEOSOMES; CARDAMOM; ALOE VERA LEAF; .ALPHA.-TOCOPHEROL ACETATE; PERILLA FRUTESCENS SEED; APPLE; SANTALUM ALBUM SEED; GREEN TEA LEAF; CHAMAEMELUM NOBILE FLOWER; CANANGA ODORATA FLOWER; ORANGE PEEL; MUSKMELON; JASMINUM OFFICINALE FLOWER; LAVANDULA ANGUSTIFOLIA SUBSP. ANGUSTIFOLIA FLOWERING TOP; RASPBERRY; POLYGONUM AVICULARE TOP; PROPANEDIOL; CETOSTEARYL ALCOHOL; PENTYLENE GLYCOL; ARACHIDYL ALCOHOL; COCO GLUCOSIDE; HYDROXYETHYL ACRYLATE/SODIUM ACRYLOYLDIMETHYL TAURATE COPOLYMER (100000 MPA.S AT 1.5%); DOCOSANOL; XANTHAN GUM; TRIETHOXYCAPRYLYLSILANE; ARACHIDYL GLUCOSIDE; PHENYLETHYL ALCOHOL; CAPRYLYL GLYCOL

SKIN REJUVENATING DAILY MOISTURIZER BROAD SPECTRUM SPF 30 SUNSCREEN

DRUG FACTS:

ACTIVE INGREDIENTS

Octinoxate 7.5%, Zinc Oxide 10.0%.

Purpose

Sunscreen

WARNINGS

For external use only. Do not use on damaged or broken skin. When using this product keep out of eyes. Rinse with water to remove. Stop use and ask a doctor if rash occurs.

Keep out of Reach of Children

DIRECTIONS

Apply to all skin exposed to the sun. *Apply liberally and evenly 15 minutes before sun exposure. *Reapply at least every 2 hours. *Use a water-resistant sunscreen if swimming or sweating. *For children under 6 months of age:

Ask a doctor.

Sun Protection Measures. Spending time in the sun increases your risk of skin cancer and early skin aging. To decrease this risk, regularly use a sunscreen with a Broad Spectrum SPF value of 15 or higher and other sun protection measures including:

- limit time in the sun, especially from 10 a.m. - 2 p.m.
- wear long-sleeved shirts, pants, hats, and sunglasses.

INACTIVE INGREDIENTS

Water (Aqua), Butyloctyl Salicylate, Glycerin, Dimethicone, Styrene/Acrylates Copolymer, Coco-Caprylate/Caprate, Caprylic/Capric Triglyceride, VP/Eicosene Copolymer, Carthamus Tinctorius Oleosomes, Elettaria Cardamomum Seed Extract, Aloe Barbadensis Leaf Juice, Tocopheryl Acetate, Perilla Frutescens Extract, Pyrus Malus (Apple) Fruit Extract, Rose Extract, Santalum Album Extract, Camellia Sinensis Leaf Extract, Anthemis Nobilis Flower Extract, Cananga Odorata Flower Extract, Citrus Aurantium Dulcis (Orange) Peel Extract, Cucumis Melo (Melon) Fruit Extract, Cucumis Sativus Fruit Extract, Jasminum Officinale Flower/Leaf Extract, Lavandula Angustifolia (Lavender) Flower/Leaf/Stem Extract, Rubus Idaeus (Raspberry) Fruit Extract, Polygonum Aviculare Extract, Vitis Vinifera Fruit Cell Extract, Propanediol, Cetearyl Alcohol, Pentylene Glycol, Arachidyl Alcohol, Polyhydroxystearic Acid, Coco-Glucoside, Hydroxyethyl Acrylate/Sodium Acryloyldimethyl Taurate Copolymer, Behenyl Alcohol, Xanthan Gum, Triethoxycaprylylsilane, Arachidyl Glucoside, Phenethyl Alcohol, Caprylyl Glycol.

OTHER INFORMATION

Protect the product in this container from excessive heat and direct sun.

PRINCIPAL DISPLAY PANEL - 29g Tube Label

DermaSet™
HOLLYWOOD SKINCARE

SPF
30

SKIN REJUVENATING

DAILY MOISTURIZER
BROAD SPECTRUM SPF 30 SUNSCREEEN

For Face & Neck

29g - Net Wt.1 Oz